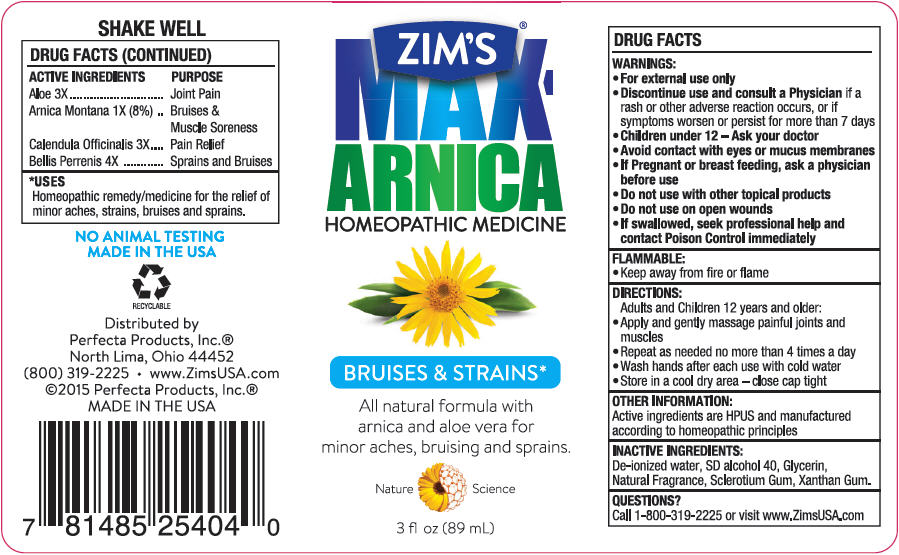 DRUG LABEL: ZIMS MAX ARNICA HOMEOPATHIC
NDC: 61561-003 | Form: GEL
Manufacturer: PERFECTA PRODUCTS, INC
Category: homeopathic | Type: HUMAN OTC DRUG LABEL
Date: 20150828

ACTIVE INGREDIENTS: ALOE VERA LEAF 3 [hp_X]/3 mL; ARNICA MONTANA 1 [hp_X]/3 mL; CALENDULA OFFICINALIS FLOWER 3 [hp_X]/3 mL; BELLIS PERENNIS 4 [hp_X]/3 mL
INACTIVE INGREDIENTS: WATER; ALCOHOL; GLYCERIN; MENTHOL, UNSPECIFIED FORM; BETASIZOFIRAN; XANTHAN GUM

ZIM'S® MAX ARNICA HOMEOPATHIC

Drug Facts

ACTIVE INGREDIENT

Active Ingredients | Purpose
Aloe 3X | Joint Pain
Arnica montana 1X (8%) | Bruises & Muscle Soreness
Calendula officinalis 3X | Pain Relief
Bellis perrenis 4X | Sprains and Bruises

Uses

According to homeopathic principles, the active ingredients in this medication help to relieve most symptoms of minor aches, strains, bruises and sprains.

Warnings

- For external use only

ASK DOCTOR

- Discontinue use and consult a Physician if a rash or other adverse reaction occurs, or if symptoms worsen or persist for more than 7 days

- Children under 12 – Ask your doctor
- Avoid contact with eyes or mucus membranes

PREGNANCY OR BREAST FEEDING

- If Pregnant or breast feeding, ask a physician before use

- Do not use with other topical products
- Do not use on open wounds
- If swallowed, seek professional help and contact Poison Control immediately

Flammable

- Keep away from fire or flame

Directions

Adults and Children 12 years and older:

- Apply and gently massage painful joints and muscles
- Repeat as needed no more than 4 times a day
- Wash hands after each use with cold water
- Store in a cool dry area – close cap tight

Other Information

Active ingredients are HPUS and manufactured according to homeopathic principles

Inactive ingredients

De-ionized water, SD alcohol 40, Glycerin, Natural Fragrance, Sclerotium Gum, Zanthan Gum

Questions?

Call 1-800-319-2225 or visit www.ZimsUSA.com

Distributed By: ©2015 PERFECTA PRODUCTS, INC.®
North Lima, Ohio 44452

PRINCIPAL DISPLAY PANEL - 89 mL Bottle Label

ZIM'S®
MAX-
ARNICA
HOMEOPATHIC MEDICINE

BRUISES & STRAINS*

All natural formula with
arnica and aloe vera for
minor aches, bruising and sprains.

Nature Science

3 fl oz (89 mL)